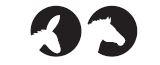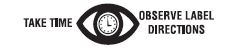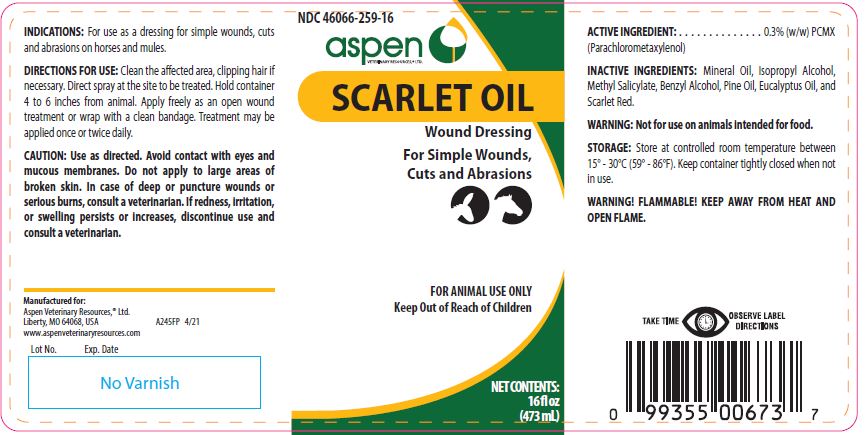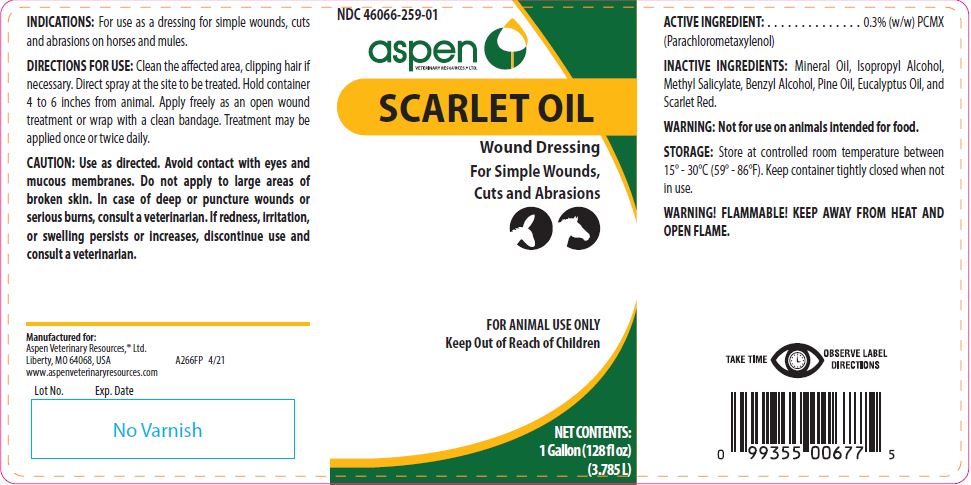 DRUG LABEL: Scarlet Oil
NDC: 46066-259 | Form: SOLUTION
Manufacturer: Aspen Veterinarian Resources
Category: animal | Type: OTC ANIMAL DRUG LABEL
Date: 20260223

ACTIVE INGREDIENTS: CHLOROXYLENOL 2.5 mg/1 mL

Scarlet Oil

PURPOSE

Wound Dressing

For Simple Wounds, Cuts and Abrasions

KEEP OUT OF REACH OF CHILDREN

FOR ANIMAL USE ONLY
Keep Out of Reach of Children

INDICATIONS:

For use as a dressing for simple wounds, cuts and abrasions on horses and mules.

DIRECTIONS FOR USE:

Clean the affected area, clipping hair if necessary. Direct spray at the site to be treated. Hold container 4 to 6 inches from animal. Apply freely as an open wound treatment or wrap with a clean bandage. Treatment may be applied once or twice daily.

CAUTION:

Use as directed. Avoid contact with eyes and mucous membranes. Do not apply to large areas of broken skin. In case of deep or puncture wounds or serious burns, consult a veterinarian. If redness, irritation, or swelling persists or increases, discontinue use and consult a veterinarian.

ACTIVE INGREDIENT:

. . . . . . . . . . . . . . 0.3% (w/w) PCMX
(Parachlorometaxylenol)

INACTIVE INGREDIENTS:

Mineral Oil, Isopropyl Alcohol, Methyl Salicylate, Benzyl Alcohol, Pine Oil, Eucalyptus Oil, and Scarlet Red.

WARNING:

Not for use on animals intended for food.

STORAGE:

Store at controlled room temperature between 15º-30ºC (59º-86ºF). Keep container tightly closed when not in use.

WARNINGS AND PRECAUTIONS

WARNING! FLAMMABLE! KEEP AWAY FROM HEAT AND OPEN FLAME.

Net Contents:

16 fl oz (473 mL) A245FP 4/21

One Gallon (3.785 L) A266FP 04/21

INFORMATION FOR OWNERS/CAREGIVERS

Manufactured for:
Aspen Veterinary Resources®, Ltd.
Liberty, MO 64068, USA
www.aspenveterinaryresources.com